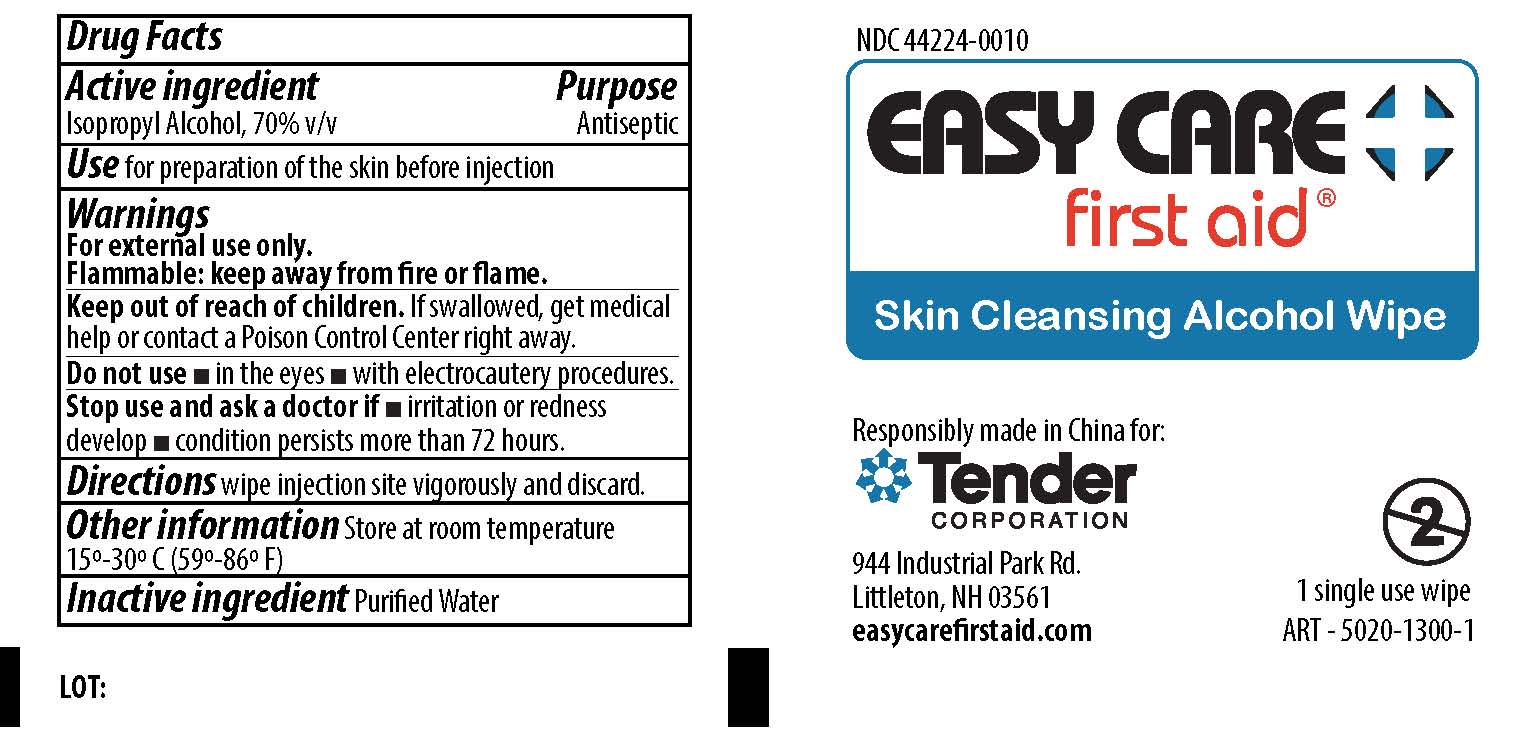 DRUG LABEL: CVS Health Home Kit
NDC: 69842-412 | Form: KIT | Route: TOPICAL
Manufacturer: CVS Pharmacy Inc
Category: otc | Type: HUMAN OTC DRUG LABEL
Date: 20190930

ACTIVE INGREDIENTS: ISOPROPYL ALCOHOL 70 mL/100 mL
INACTIVE INGREDIENTS: WATER

CVS Health Home Kit

Active Ingredient

Isopropyl Alcohol, 70% v/v

Purpose

Antiseptic

Use

For preparation of skin before injection.

Warnings

For external use only.

Flammable - keep away from fire or flame

Do not use

- in the eyes
- with electrocautery procedures

Stop use and ask a doctor if

- irritation and redness develop
- condition persists for more than 72 hours

KEEP OUT OF REACH OF CHILDREN

If swallowed, get medical help or contact a Poison Control Center right away.

Directions

Wipe Injection site vigorously and discard.

Other Information

Store at room temperature 15-30 degree Celsius (59-86 degree Fahrenheit)

Inactive Ingredient

purified water

PACKAGE LABEL

Easy Care First Aid® Skin Cleansing Alcohol Wipe

Responsibly made in China for:

Tender Corporation

944 Industrial Park Rd.

Littleton, NH 03561
easycarefirstaid.com

1 single use wipe